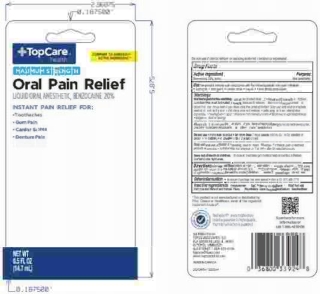 DRUG LABEL: Topcare
NDC: 36800-443 | Form: LIQUID
Manufacturer: Topco Associates LLC
Category: otc | Type: HUMAN OTC DRUG LABEL
Date: 20250812

ACTIVE INGREDIENTS: BENZOCAINE 20 g/100 g
INACTIVE INGREDIENTS: POLYETHYLENE GLYCOL 400; SACCHARIN SODIUM; PROPYLENE GLYCOL; METHYLPARABEN; BENZYL ALCOHOL; WATER; FD&C RED NO. 40; D&C YELLOW NO. 10; FD&C BLUE NO. 1

5820344 Top Care Oral Pain Relief Liquid

Drug Facts

Active ingredient

Benzocaine 20.0% (w/w)

Purpose

Oral anesthetic

Uses

Temporarily relieves pain associated with the following mouth and gum irritations:

- toothache
- sore gums
- canker sores
- braces
- minor dental procedures

Warnings

Allergy Alert: do not use this product if you have a history of allergy to local anesthetics such as procaine, butacaine, benzocaine or other "caine" anesthetics

When using this product

- avoid contact with eyes
- do not exceed recommended dosage
- do not use for more than 7 days unless directed by a dentist or doctor

Stop use and ask doctor or dentist if

- sore mouth symptoms do not improve in 7 days
- irritation, pain or redness persists or worsens
- swelling, rash or fever develops

Keep out of reach of children. If swallowed, get medical help or contact a Poison Control Center right away.

Directions

- Adults and children 2 years of age and older:
- apply to affected area using applicator tip
- use up to 4 times daily or as directed by a dentist or doctor
- children under 12 years of age should be supervised in the use of this product
- children under 2 years of age: consult a dentist or doctor

Other information

- do not use if package has been opened
- store at 20 - 25°C (68-77°F)

INACTIVE INGREDIENT

Inactive ingredients Benzyl Alcohol, D&C Yellow no. 10, FD&C Blue no. 1, FD&C Red no. 40, Methylparaben, Natural and Artifical Flavor, Polyethylene Glycol, Propylene Glycol, Sodium Saccharin, Water

DISTRIBUTED BY TOPCO ASSOCIATES LLC

ELK GROVE VILLAGE, IL 60007

QUESTIONS?

1-888-423-0139

topcare@topco.com

MADE IN CANADA